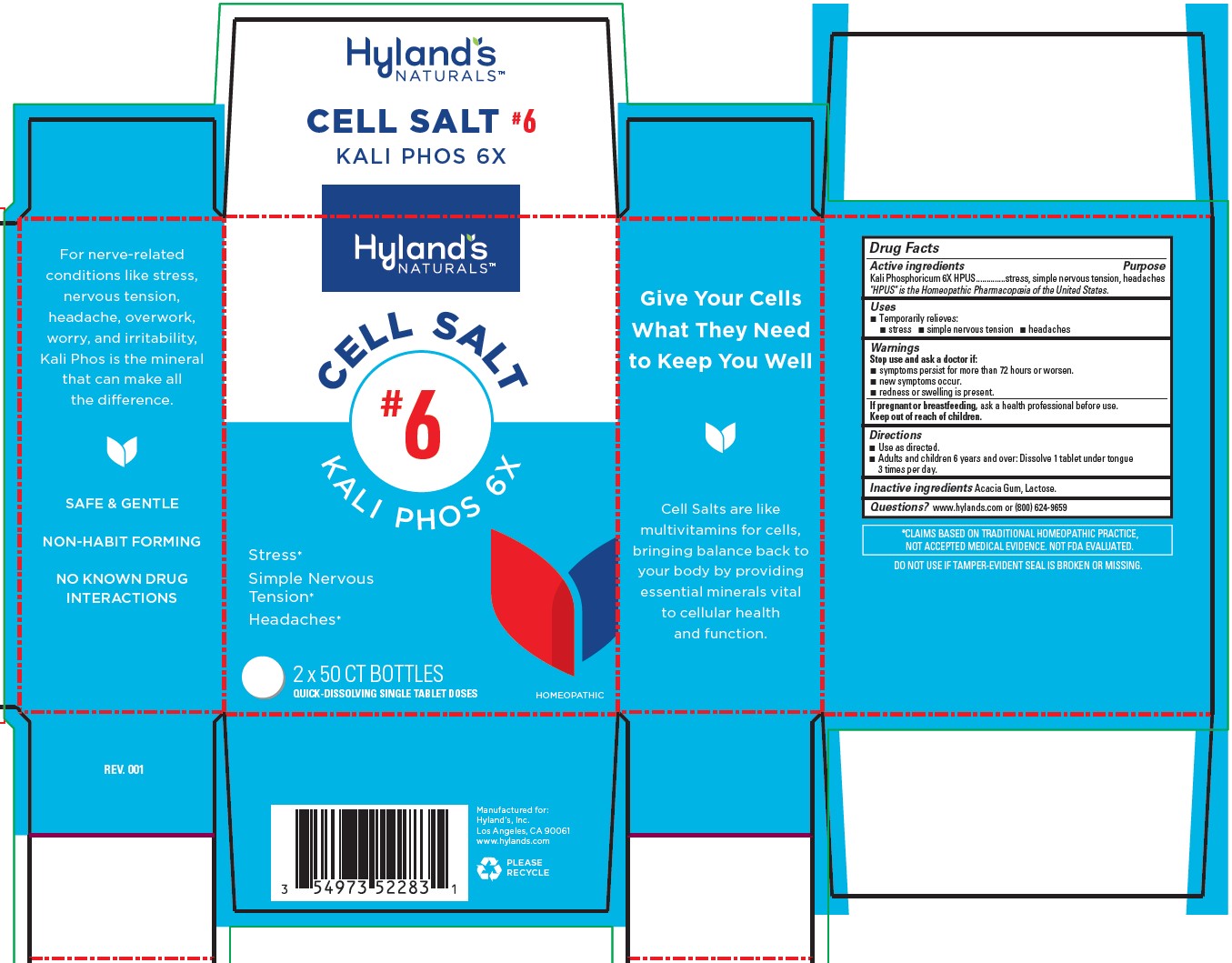 DRUG LABEL: Kali Phos
NDC: 54973-4077 | Form: TABLET
Manufacturer: Hyland’s Inc.
Category: homeopathic | Type: HUMAN OTC DRUG LABEL
Date: 20221212

ACTIVE INGREDIENTS: DIBASIC POTASSIUM PHOSPHATE 6 [hp_X]/1 1
INACTIVE INGREDIENTS: ACACIA; LACTOSE MONOHYDRATE

Cell Salt # 6 Kali Phos 6X

PURPOSE

Temporarily relieves stress, simple nervous tension, headaches

Drug Facts

Active ingredients

Active ingredients | Purpose
Kali Phosphoricum 6X HPUS | stress, simple nervous tension, headaches

"HPUS" is the Homeopathic Pharmacopoeia of the United States.

Uses

■ Temporarily relieves:
■ stress ■ simple nervous tension ■ headaches

Warnings

Stop use and ask a doctor if

■ symptoms persist for more than 72 hours or worsen.
■ new symptoms occur.
■ redness or swelling is present.

If pregnant or breastfeeding

ask a health professional before use.

Directions

■ Use as directed.
■ Adults and children 6 years and over: Dissolve 1 tablet under tongue 3 times per day.

Inactive ingredients

Acacia Gum, Lactose.

Questions?

www.hylands.com or (800) 624-9659

PACKAGING LABEL - 2 x 50 TABLET BOTTLE CARTON

Hyland's

NATURALS™

CELL SALT

# 6

KALI PHOS 6X

Stress*

Simple Nervous

Tension*

Headaches*

2 x 50 CT BOTTLES

QUICK-DISSOLVING SINGLE TABLET DOSES

HOMEOPATHIC